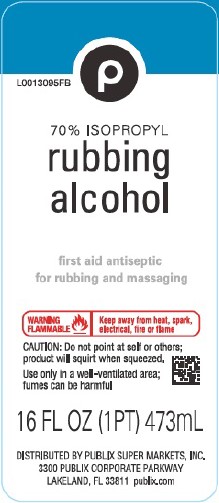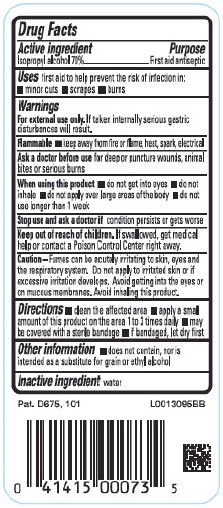 DRUG LABEL: Isopropyl Alcohol
NDC: 56062-810 | Form: LIQUID
Manufacturer: Publix Super Markets, Inc.
Category: otc | Type: HUMAN OTC DRUG LABEL
Date: 20260205

ACTIVE INGREDIENTS: ISOPROPYL ALCOHOL 70 mL/100 mL
INACTIVE INGREDIENTS: WATER

Publix 810.003/810AA
70% Isopropyl Alcohol

Active Ingredient

Isopropyl alcohol 70%

Purpose

First aid antiseptic

Uses

First aid to help prevent the risk of infection in:

- minor cuts
- scrapes
- burns

Warnings

For external use only. If taken internally serious gstric disturbances will result.

Flammable Keep away from fire or flame, heat, spark, electrical

Ask a doctor before use

for deep or puncture wounds, animal bites or serious burns

When using this product if

- do not get into eyes
- do not inhale
- do not apply over large areas of the body
- do not use longer than 1 week

Stop use and ask a doctor if

condition persists or gets worse

Keep out of reach of children.

If swallowed, get medical help or contact a Poison Control Center right away.

Caution

Fumes can be acutely irritating to skin, eyes and the respiratory system. Do not apply to irritated skin or if excessive irriataion develops. Avoid getting into the eyes or mucous membranes. Avoid inhaling this product.

Directions

- clean the affected area
- apply a small amount of this product on the area 1 to 3 times daily
- may be covered with a sterile bandage
- if bandaged, let dry first

Other information

- does not contain, nor is intended as a substitute for grain or ethyl alcohol

Inactive ingredient

water

Principal display panel

P

70% isorpopyl

rubbing alcohol

first aid antiseptic

for rubbing and massaging

WARNING FLAMMABLE Keep away from heat, spark, electrical, fire or flame

CAUTION: Do not point at self or others; product will squirt when squeezed.

Use only in a well-ventilated area; fumes may be harmful

16 FL OZ (1 PT) 473 mL

DISTRIBUTED BY PUBLIX SUPER MARKETS, INC.

3300 PUBLIX CORPORATE PARKWAY

LAKELAND, FL 33811 publix.com

Pat. D675, 101